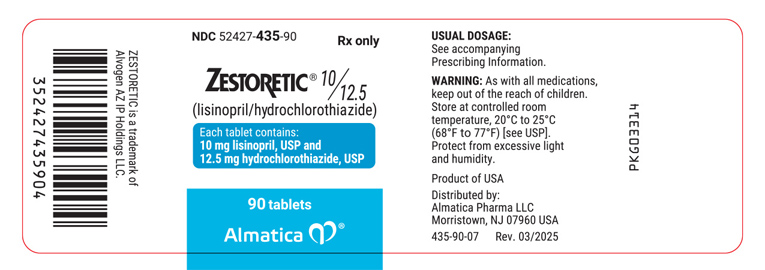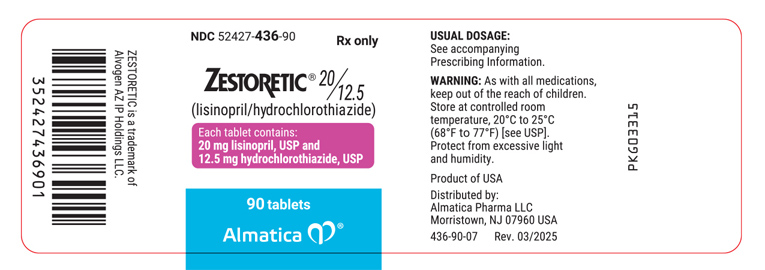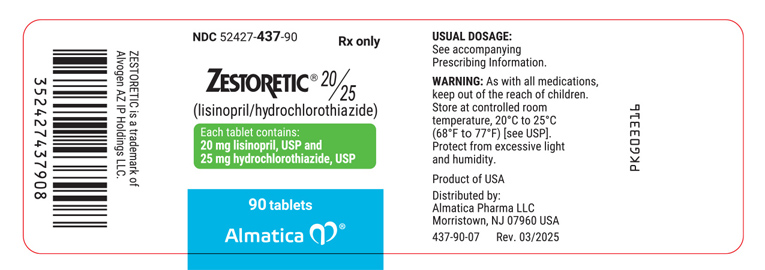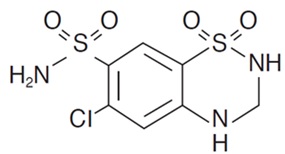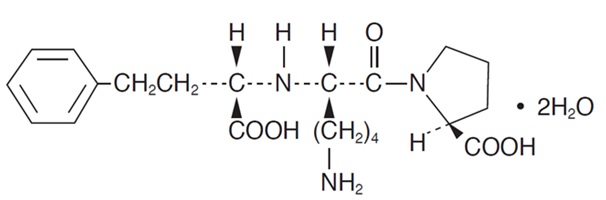 DRUG LABEL: Zestoretic
NDC: 52427-435 | Form: TABLET
Manufacturer: Almatica Pharma Inc.
Category: prescription | Type: HUMAN PRESCRIPTION DRUG LABEL
Date: 20250331

ACTIVE INGREDIENTS: LISINOPRIL 10 mg/1 1; HYDROCHLOROTHIAZIDE 12.5 mg/1 1
INACTIVE INGREDIENTS: DIBASIC CALCIUM PHOSPHATE DIHYDRATE; MAGNESIUM STEARATE; MANNITOL; FERRIC OXIDE RED; STARCH, CORN; FERRIC OXIDE YELLOW

WARNING: FETAL TOXICITY

See full prescribing information for complete boxed warning.

- When pregnancy is detected, discontinue ZESTORETIC as soon as possible.
- Drugs that act directly on the renin-angiotensin system can cause injury and death to the developing fetus. See Warnings: Fetal Toxicity.

DESCRIPTION

ZESTORETIC® (Lisinopril and Hydrochlorothiazide) combines an angiotensin converting enzyme inhibitor, lisinopril, and a diuretic, hydrochlorothiazide.

Lisinopril, USP a synthetic peptide derivative, is an oral long-acting angiotensin converting enzyme inhibitor. It is chemically described as (S)-1-[N2-(1-carboxy-3-phenylpropyl)-L-lysyl]-L-proline dihydrate. Its empirical formula is C21H31N3O5 . 2H2O and its structural formula is:

Lisinopril, USP is a white to off-white, crystalline powder, with a molecular weight of 441.53. It is soluble in water, sparingly soluble in methanol, and practically insoluble in ethanol.

Hydrochlorothiazide, USP is 6-chloro-3,4-dihydro-2H-1,2,4-benzothiadiazine-7-sulfonamide 1,1-dioxide. Its empirical formula is C7H8ClN3O4S2 and its structural formula is:

Hydrochlorothiazide, USP is a white, or practically white, crystalline powder with a molecular weight of 297.72, which is slightly soluble in water, but freely soluble in sodium hydroxide solution.

ZESTORETIC is available for oral use in three tablet combinations of lisinopril, USP with hydrochlorothiazide, USP: ZESTORETIC 10-12.5 containing 10 mg lisinopril, USP and 12.5 mg hydrochlorothiazide, USP; ZESTORETIC 20-12.5 containing 20 mg lisinopril, USP and 12.5 mg hydrochlorothiazide, USP; and, ZESTORETIC 20-25 containing 20 mg lisinopril, USP and 25 mg hydrochlorothiazide, USP.

Inactive Ingredients:

10-12.5 Tablets - calcium phosphate, magnesium stearate, mannitol, red ferric oxide, corn starch, yellow ferric oxide.

20-12.5 Tablets - calcium phosphate, magnesium stearate, mannitol, corn starch.

20-25 Tablets - calcium phosphate, magnesium stearate, mannitol, red ferric oxide, corn starch, yellow ferric oxide.

CLINICAL PHARMACOLOGY

Lisinopril and Hydrochlorothiazide

As a result of its diuretic effects, hydrochlorothiazide increases plasma renin activity, increases aldosterone secretion, and decreases serum potassium. Administration of lisinopril blocks the renin-angiotensin aldosterone axis and tends to reverse the potassium loss associated with the diuretic.

In clinical studies, the extent of blood pressure reduction seen with the combination of lisinopril and hydrochlorothiazide was approximately additive. The ZESTORETIC 10-12.5 combination worked equally well in black and white patients. The ZESTORETIC 20-12.5 and ZESTORETIC 20-25 combinations appeared somewhat less effective in black patients, but relatively few black patients were studied. In most patients, the antihypertensive effect of ZESTORETIC was sustained for at least 24 hours.

In a randomized, controlled comparison, the mean antihypertensive effects of ZESTORETIC 20-12.5 and ZESTORETIC 20-25 were similar, suggesting that many patients who respond adequately to the latter combination may be controlled with ZESTORETIC 20-12.5 (see DOSAGE AND ADMINISTRATION).

Concomitant administration of lisinopril and hydrochlorothiazide has little or no effect on the bioavailability of either drug. The combination tablet is bioequivalent to concomitant administration of the separate entities.

Lisinopril

Mechanism of Action

Lisinopril inhibits angiotensin-converting enzyme (ACE) in human subjects and animals. ACE is a peptidyl dipeptidase that catalyzes the conversion of angiotensin I to the vasoconstrictor substance, angiotensin II. Angiotensin II also stimulates aldosterone secretion by the adrenal cortex. Inhibition of ACE results in decreased plasma angiotensin II which leads to decreased vasopressor activity and to decreased aldosterone secretion. The latter decrease may result in a small increase of serum potassium. Removal of angiotensin II negative feedback on renin secretion leads to increased plasma renin activity. In hypertensive patients with normal renal function treated with lisinopril alone for up to 24 weeks, the mean increase in serum potassium was less than 0.1 mEq/L; however, approximately 15 percent of patients had increases greater than 0.5 mEq/L and approximately six percent had a decrease greater than 0.5 mEq/L. In the same study, patients treated with lisinopril plus a thiazide diuretic showed essentially no change in serum potassium (see PRECAUTIONS).

ACE is identical to kininase, an enzyme that degrades bradykinin. Whether increased levels of bradykinin, a potent vasodepressor peptide, play a role in the therapeutic effects of lisinopril remains to be elucidated.

While the mechanism through which lisinopril lowers blood pressure is believed to be primarily suppression of the renin-angiotensin-aldosterone system, lisinopril is antihypertensive even in patients with low-renin hypertension. Although lisinopril was antihypertensive in all races studied, black hypertensive patients (usually a low-renin hypertensive population) had a smaller average response to lisinopril monotherapy than nonblack patients.

Pharmacokinetics and Metabolism

Following oral administration of lisinopril, peak serum concentrations occur within about 7 hours. Declining serum concentrations exhibit a prolonged terminal phase which does not contribute to drug accumulation. This terminal phase probably represents saturable binding to ACE and is not proportional to dose. Lisinopril does not appear to be bound to other serum proteins.

Lisinopril does not undergo metabolism and is excreted unchanged entirely in the urine. Based on urinary recovery, the mean extent of absorption of lisinopril is approximately 25 percent, with large intersubject variability (6% to 60%) at all doses tested (5 mg to 80 mg). Lisinopril absorption is not influenced by the presence of food in the gastrointestinal tract.

Upon multiple dosing, lisinopril exhibits an effective half-life of accumulation of 12 hours.

Impaired renal function decreases elimination of lisinopril, which is excreted principally through the kidneys, but this decrease becomes clinically important only when the glomerular filtration rate is below 30 mL/min. Above this glomerular filtration rate, the elimination half-life is little changed. With greater impairment, however, peak and trough lisinopril levels increase, time to peak concentration increases and time to attain steady state is prolonged. Older patients, on average, have (approximately doubled) higher blood levels and area under the plasma concentration time curve (AUC) than younger patients (see DOSAGE AND ADMINISTRATION). In a multiple dose pharmacokinetic study in elderly versus young hypertensive patients using the lisinopril/hydrochlorothiazide combination, the AUC increased approximately 120% for lisinopril and approximately 80% for hydrochlorothiazide in older patients. Lisinopril can be removed by hemodialysis.

Studies in rats indicate that lisinopril crosses the blood-brain barrier poorly. Multiple doses of lisinopril in rats do not result in accumulation in any tissues; however, milk of lactating rats contains radioactivity following administration of ^14C lisinopril. By whole body autoradiography, radioactivity was found in the placenta following administration of labeled drug to pregnant rats, but none was found in the fetuses.

Pharmacodynamics

Administration of lisinopril to patients with hypertension results in a reduction of supine and standing blood pressure to about the same extent with no compensatory tachycardia. Symptomatic postural hypotension is usually not observed although it can occur and should be anticipated in volume and/or salt-depleted patients (see WARNINGS).

In most patients studied, onset of antihypertensive activity was seen at one hour after oral administration of an individual dose of lisinopril, with peak reduction of blood pressure achieved by six hours.

In some patients achievement of optimal blood pressure reduction may require two to four weeks of therapy.

At recommended single daily doses, antihypertensive effects have been maintained for at least 24 hours, after dosing, although the effect at 24 hours was substantially smaller than the effect six hours after dosing.

The antihypertensive effects of lisinopril have continued during long-term therapy. Abrupt withdrawal of lisinopril has not been associated with a rapid increase in blood pressure; nor with a significant overshoot of pretreatment blood pressure.

In hemodynamic studies in patients with essential hypertension, blood pressure reduction was accompanied by a reduction in peripheral arterial resistance with little or no change in cardiac output and in heart rate. In a study in nine hypertensive patients, following administration of lisinopril, there was an increase in mean renal blood flow that was not significant. Data from several small studies are inconsistent with respect to the effect of lisinopril on glomerular filtration rate in hypertensive patients with normal renal function, but suggest that changes, if any, are not large.

In patients with renovascular hypertension lisinopril has been shown to be well tolerated and effective in controlling blood pressure (see PRECAUTIONS).

Hydrochlorothiazide

The mechanism of the antihypertensive effect of thiazides is unknown. Thiazides do not usually affect normal blood pressure.

Hydrochlorothiazide is a diuretic and antihypertensive. It affects the distal renal tubular mechanism of electrolyte reabsorption. Hydrochlorothiazide increases excretion of sodium and chloride in approximately equivalent amounts. Natriuresis may be accompanied by some loss of potassium and bicarbonate.

After oral use diuresis begins within two hours, peaks in about four hours and lasts about 6 to 12 hours.

Hydrochlorothiazide is not metabolized but is eliminated rapidly by the kidney. When plasma levels have been followed for at least 24 hours, the plasma half-life has been observed to vary between 5.6 and 14.8 hours. At least 61 percent of the oral dose is eliminated unchanged within 24 hours. Hydrochlorothiazide crosses the placental but not the blood-brain barrier.

INDICATIONS AND USAGE

ZESTORETIC is indicated for the treatment of hypertension, to lower blood pressure. Lowering blood pressure lowers the risk of fatal and non-fatal cardiovascular events, primarily strokes and myocardial infarctions. These benefits have been seen in controlled trials of antihypertensive drugs from a wide variety of pharmacologic classes including lisinopril and hydrochlorothiazide.

Control of high blood pressure should be part of comprehensive cardiovascular risk management, including, as appropriate, lipid control, diabetes management, antithrombotic therapy, smoking cessation, exercise, and limited sodium intake. Many patients will require more than 1 drug to achieve blood pressure goals. For specific advice on goals and management, see published guidelines, such as those of the National High Blood Pressure Education Program’s Joint National Committee on Prevention, Detection, Evaluation, and Treatment of High Blood Pressure (JNC).

Numerous antihypertensive drugs, from a variety of pharmacologic classes and with different mechanisms of action, have been shown in randomized controlled trials to reduce cardiovascular morbidity and mortality, and it can be concluded that it is blood pressure reduction, and not some other pharmacologic property of the drugs, that is largely responsible for those benefits. The largest and most consistent cardiovascular outcome benefit has been a reduction in the risk of stroke, but reductions in myocardial infarction and cardiovascular mortality also have been seen regularly.

Elevated systolic or diastolic pressure causes increased cardiovascular risk, and the absolute risk increase per mmHg is greater at higher blood pressures, so that even modest reductions of severe hypertension can provide substantial benefit. Relative risk reduction from blood pressure reduction is similar across populations with varying absolute risk, so the absolute benefit is greater in patients who are at higher risk independent of their hypertension (for example, patients with diabetes or hyperlipidemia), and such patients would be expected to benefit from more aggressive treatment to a lower blood pressure goal.

Some antihypertensive drugs have smaller blood pressure effects (as monotherapy) in black patients, and many antihypertensive drugs have additional approved indications and effects (e.g., on angina, heart failure, or diabetic kidney disease). These considerations may guide selection of therapy.

These fixed-dose combinations are not indicated for initial therapy (see DOSAGE AND ADMINISTRATION).

In using ZESTORETIC, consideration should be given to the fact that an angiotensin-converting enzyme inhibitor, captopril, has caused agranulocytosis, particularly in patients with renal impairment or collagen vascular disease, and that available data are insufficient to show that lisinopril does not have a similar risk (see WARNINGS).

In considering the use of ZESTORETIC, it should be noted that ACE inhibitors have been associated with a higher rate of angioedema in black than in nonblack patients (see WARNINGS, Lisinopril).

CONTRAINDICATIONS

ZESTORETIC is contraindicated in patients who are hypersensitive to this product and in patients with a history of angioedema related to previous treatment with an angiotensin-converting enzyme inhibitor and in patients with hereditary or idiopathic angioedema. Because of the hydrochlorothiazide component, this product is contraindicated in patients with anuria or hypersensitivity to other sulfonamide-derived drugs.

ZESTORETIC is contraindicated in combination with a neprilysin inhibitor (e.g., sacubitril). Do not administer ZESTORETIC within 36 hours of switching to or from sacubitril/valsartan, a neprilysin inhibitor (see WARNINGS).
Do not co-administer aliskiren with ZESTORETIC in patients with diabetes (see PRECAUTIONS, Drug Interactions).

WARNINGS

Lisinopril

Anaphylactoid and Possibly Related Reactions: Presumably because angiotensin-converting enzyme inhibitors affect the metabolism of eicosanoids and polypeptides, including endogenous bradykinin, patients receiving ACE inhibitors (including ZESTORETIC) may be subject to a variety of adverse reactions, some of them serious.

Head and Neck Angioedema: Angioedema of the face, extremities, lips, tongue, glottis and/or larynx has been reported in patients treated with angiotensin-converting enzyme inhibitors, including lisinopril. This may occur at any time during treatment. ACE inhibitors have been associated with a higher rate of angioedema in black than in nonblack patients. ZESTORETIC should be promptly discontinued and the appropriate therapy and monitoring should be provided until complete and sustained resolution of signs and symptoms has occurred. Even in those instances where swelling of only the tongue is involved, without respiratory distress, patients may require prolonged observation since treatment with antihistamines and corticosteroids may not be sufficient. Very rarely, fatalities have been reported due to angioedema associated with laryngeal edema or tongue edema. Patients with involvement of the tongue, glottis or larynx are likely to experience airway obstruction, especially those with a history of airway surgery. Where there is involvement of the tongue, glottis or larynx, likely to cause airway obstruction, subcutaneous epinephrine solution 1:1000 (0.3 mL to 0.5 mL) and/or measures necessary to ensure a patent airway should be promptly provided (see ADVERSE REACTIONS).

Patients receiving coadministration of ACE inhibitor and mTOR (mammalian target of rapamycin) inhibitor (e.g., temsirolimus, sirolimus, everolimus) therapy or a neprilysin inhibitor may be at increased risk for angioedema (see PRECAUTIONS).

Intestinal Angioedema: Intestinal angioedema has been reported in patients treated with ACE inhibitors. These patients presented with abdominal pain (with or without nausea or vomiting); in some cases there was no prior history of facial angioedema and C-1 esterase levels were normal. The angioedema was diagnosed by procedures including abdominal CT scan or ultrasound, or at surgery, and symptoms resolved after stopping the ACE inhibitor. Intestinal angioedema should be included in the differential diagnosis of patients on ACE inhibitors presenting with abdominal pain.

Patients with a history of angioedema unrelated to ACE inhibitor therapy may be at increased risk of angioedema while receiving an ACE inhibitor (see also INDICATIONS AND USAGE and CONTRAINDICATIONS).

Anaphylactoid Reactions During Desensitization: Two patients undergoing desensitizing treatment with hymenoptera venom while receiving ACE inhibitors sustained life-threatening anaphylactoid reactions. In the same patients, these reactions were avoided when ACE inhibitors were temporarily withheld, but they reappeared upon inadvertent rechallenge.

Anaphylactoid Reactions during Membrane Exposure: Thiazide-containing combination products are not recommended in patients with severe renal dysfunction. Sudden and potentially life-threatening anaphylactoid reactions have been reported in some patients dialyzed with high-flux membranes (e.g., AN69®*) and treated concomitantly with an ACE inhibitor. In such patients, dialysis must be stopped immediately, and aggressive therapy for anaphylactoid reactions must be initiated. Symptoms have not been relieved by antihistamines in these situations. In these patients, consideration should be given to using a different type of dialysis membrane or a different class of antihypertensive agent. Anaphylactoid reactions have also been reported in patients undergoing low-density lipoprotein apheresis with dextran sulfate absorption.

Hypotension and Related Effects: Excessive hypotension was rarely seen in uncomplicated hypertensive patients but is a possible consequence of lisinopril use in salt/volume-depleted persons such as those treated vigorously with diuretics or patients on dialysis (see PRECAUTIONS, Drug Interactions and ADVERSE REACTIONS).

Syncope has been reported in 0.8 percent of patients receiving ZESTORETIC. In patients with hypertension receiving lisinopril alone, the incidence of syncope was 0.1 percent. The overall incidence of syncope may be reduced by proper titration of the individual components (see PRECAUTIONS, Drug Interactions, ADVERSE REACTIONS and DOSAGE AND ADMINISTRATION).

In patients with severe congestive heart failure, with or without associated renal insufficiency, excessive hypotension has been observed and may be associated with oliguria and/or progressive azotemia, and rarely with acute renal failure and/or death. Because of the potential fall in blood pressure in these patients, therapy should be started under very close medical supervision. Such patients should be followed closely for the first two weeks of treatment and whenever the dose of lisinopril and/or diuretic is increased. Similar considerations apply to patients with ischemic heart or cerebrovascular disease in whom an excessive fall in blood pressure could result in a myocardial infarction or cerebrovascular accident.

If hypotension occurs, the patient should be placed in the supine position and, if necessary, receive an intravenous infusion of normal saline. A transient hypotensive response is not a contraindication to further doses which usually can be given without difficulty once the blood pressure has increased after volume expansion.

Leukopenia/Neutropenia/Agranulocytosis: Another angiotensin-converting enzyme inhibitor, captopril, has been shown to cause agranulocytosis and bone marrow depression, rarely in uncomplicated patients but more frequently in patients with renal impairment, especially if they also have a collagen vascular disease. Available data from clinical trials of lisinopril are insufficient to show that lisinopril does not cause agranulocytosis at similar rates. Marketing experience has revealed rare cases of leukopenia/neutropenia and bone marrow depression in which a causal relationship to lisinopril cannot be excluded. Periodic monitoring of white blood cell counts in patients with collagen vascular disease and renal disease should be considered.

Hepatic Failure: Rarely, ACE inhibitors have been associated with a syndrome that starts with cholestatic jaundice or hepatitis and progresses to fulminant hepatic necrosis and (sometimes) death. The mechanism of this syndrome is not understood. Patients receiving ACE inhibitors who develop jaundice or marked elevations of hepatic enzymes should discontinue the ACE inhibitor and receive appropriate medical follow-up.

Fetal Toxicity

Pregnancy category D
Use of drugs that act on the renin-angiotensin system during the second and third trimesters of pregnancy reduces fetal renal function and increases fetal and neonatal morbidity and death. Resulting oligohydramnios can be associated with fetal lung hypoplasia and skeletal deformations. Potential neonatal adverse effects include skull hypoplasia, anuria, hypotension, renal failure, and death. When pregnancy is detected, discontinue ZESTORETIC as soon as possible. These adverse outcomes are usually associated with use of these drugs in the second and third trimester of pregnancy. Most epidemiologic studies examining fetal abnormalities after exposure to antihypertensive use in the first trimester have not distinguished drugs affecting the renin-angiotensin system from other antihypertensive agents. Appropriate management of maternal hypertension during pregnancy is important to optimize outcomes for both mother and fetus.

In the unusual case that there is no appropriate alternative to therapy with drugs affecting the renin-angiotensin system for a particular patient, apprise the mother of the potential risk to the fetus. Perform serial ultrasound examinations to assess the intra-amniotic environment. If oligohydramnios is observed, discontinue ZESTORETIC, unless it is considered lifesaving for the mother. Fetal testing may be appropriate, based on the week of pregnancy. Patients and physicians should be aware, however, that oligohydramnios may not appear until after the fetus has sustained irreversible injury. Closely observe infants with histories of in utero exposure to ZESTORETIC for hypotension, oliguria, and hyperkalemia. (See Precautions, Pediatric Use).

No teratogenic effects of lisinopril were seen in studies of pregnant rats, mice, and rabbits. On a mg/kg basis, the doses used were up to 625 times (in mice), 188 times (in rats), and 0.6 times (in rabbits) the maximum recommended human dose.

Lisinopril and Hydrochlorothiazide

Teratogenicity studies were conducted in mice and rats with up to 90 mg/kg/day of lisinopril (56 times the maximum recommended human dose) in combination with 10 mg/kg/day of hydrochlorothiazide (2.5 times the maximum recommended human dose). Maternal or fetotoxic effects were not seen in mice with the combination. In rats decreased maternal weight gain and decreased fetal weight occurred down to 3/10 mg/kg/day (the lowest dose tested). Associated with the decreased fetal weight was a delay in fetal ossification. The decreased fetal weight and delay in fetal ossification were not seen in saline-supplemented animals given 90/10 mg/kg/day.

When used in pregnancy, during the second and third trimesters, ACE inhibitors can cause injury and even death to the developing fetus. When pregnancy is detected, discontinue ZESTORETIC as soon as possible (see Lisinopril, Fetal Toxicity).

Hydrochlorothiazide

Acute Myopia and Secondary Angle-Closure Glaucoma: Hydrochlorothiazide, a sulfonamide, can cause an idiosyncratic reaction, resulting in acute transient myopia and acute angle-closure glaucoma. Symptoms include acute onset of decreased visual acuity or ocular pain and typically occur within hours to weeks of drug initiation. Untreated acute angle-closure glaucoma can lead to permanent vision loss. The primary treatment is to discontinue hydrochlorothiazide as rapidly as possible. Prompt medical or surgical treatments may need to be considered if the intraocular pressure remains uncontrolled. Risk factors for developing acute angle-closure glaucoma may include a history of sulfonamide or penicillin allergy.

Teratogenic Effects: Reproduction studies in the rabbit, the mouse and the rat at doses up to 100 mg/kg/day (50 times the human dose) showed no evidence of external abnormalities of the fetus due to hydrochlorothiazide. Hydrochlorothiazide given in a two-litter study in rats at doses of 4 mg/kg/day to 5.6 mg/kg/day (approximately 1 to 2 times the usual daily human dose) did not impair fertility or produce birth abnormalities in the offspring. Thiazides cross the placental barrier and appear in cord blood.

Nonteratogenic Effects: These may include fetal or neonatal jaundice, thrombocytopenia, and possibly other adverse reactions have occurred in the adult.

Hydrochlorothiazide

Thiazides should be used with caution in severe renal disease. In patients with renal disease, thiazides may precipitate azotemia. Cumulative effects of the drug may develop in patients with impaired renal function.

Thiazides should be used with caution in patients with impaired hepatic function or progressive liver disease, since minor alterations of fluid and electrolyte balance may precipitate hepatic coma.

Sensitivity reactions may occur in patients with or without a history of allergy or bronchial asthma.

The possibility of exacerbation or activation of systemic lupus erythematosus has been reported.

Lithium generally should not be given with thiazides (see PRECAUTIONS, Drug Interactions, Lisinopril and Hydrochlorothiazide).

PRECAUTIONS

General

Lisinopril

Aortic Stenosis/Hypertrophic Cardiomyopathy: As with all vasodilators, lisinopril should be given with caution to patients with obstruction in the outflow tract of the left ventricle.

Impaired Renal Function: As a consequence of inhibiting the renin-angiotensin-aldosterone system, changes in renal function may be anticipated in susceptible individuals. In patients with severe congestive heart failure whose renal function may depend on the activity of the renin-angiotensin-aldosterone system, treatment with angiotensin-converting enzyme inhibitors, including lisinopril, may be associated with oliguria and/or progressive azotemia and rarely with acute renal failure and/or death.

In hypertensive patients with unilateral or bilateral renal artery stenosis, increases in blood urea nitrogen and serum creatinine may occur. Experience with another angiotensin-converting enzyme inhibitor suggests that these increases are usually reversible upon discontinuation of lisinopril and/or diuretic therapy. In such patients renal function should be monitored during the first few weeks of therapy.

Some hypertensive patients with no apparent pre-existing renal vascular disease have developed increases in blood urea and serum creatinine, usually minor and transient, especially when lisinopril has been given concomitantly with a diuretic. This is more likely to occur in patients with pre-existing renal impairment. Dosage reduction of lisinopril and/or discontinuation of the diuretic may be required.

Evaluation of the hypertensive patient should always include assessment of renal function (see DOSAGE AND ADMINISTRATION).

Hyperkalemia: In clinical trials hyperkalemia (serum potassium greater than 5.7 mEq/L) occurred in approximately 1.4 percent of hypertensive patients treated with lisinopril plus hydrochlorothiazide. In most cases these were isolated values which resolved despite continued therapy. Hyperkalemia was not a cause of discontinuation of therapy. Risk factors for the development of hyperkalemia include renal insufficiency, diabetes mellitus, and the concomitant use of potassium-sparing diuretics, potassium supplements and/or potassium-containing salt substitutes. Hyperkalemia can cause serious, sometimes fatal, arrhythmias. ZESTORETIC should be used cautiously, if at all, with these agents and with frequent monitoring of serum potassium (see PRECAUTIONS, Drug Interactions).

Cough: Presumably due to the inhibition of the degradation of endogenous bradykinin, persistent nonproductive cough has been reported with all ACE inhibitors, almost always resolving after discontinuation of therapy. ACE inhibitor-induced cough should be considered in the differential diagnosis of cough.

Surgery/Anesthesia: In patients undergoing major surgery or during anesthesia with agents that produce hypotension, lisinopril may block angiotensin II formation secondary to compensatory renin release. If hypotension occurs and is considered to be due to this mechanism, it can be corrected by volume expansion.

Hydrochlorothiazide

Periodic determination of serum electrolytes to detect possible electrolyte imbalance should be performed at appropriate intervals.

All patients receiving thiazide therapy should be observed for clinical signs of fluid or electrolyte imbalance: namely, hyponatremia, hypochloremic alkalosis, and hypokalemia. Serum and urine electrolyte determinations are particularly important when the patient is vomiting excessively or receiving parenteral fluids. Warning signs or symptoms of fluid and electrolyte imbalance, irrespective of cause, include dryness of mouth, thirst, weakness, lethargy, drowsiness, restlessness, confusion, seizures, muscle pains or cramps, muscular fatigue, hypotension, oliguria, tachycardia, and gastrointestinal disturbances such as nausea and vomiting.

Hypokalemia may develop, especially with brisk diuresis, when severe cirrhosis is present, or after prolonged therapy.

Interference with adequate oral electrolyte intake will also contribute to hypokalemia. Hypokalemia may cause cardiac arrhythmia and may also sensitize or exaggerate the response of the heart to the toxic effects of digitalis (e.g., increased ventricular irritability). Because lisinopril reduces the production of aldosterone, concomitant therapy with lisinopril attenuates the diuretic-induced potassium loss (see PRECAUTIONS, Drug Interactions, Agents Increasing Serum Potassium).

Although any chloride deficit is generally mild and usually does not require specific treatment, except under extraordinary circumstances (as in liver disease or renal disease), chloride replacement may be required in the treatment of metabolic alkalosis.

Dilutional hyponatremia may occur in edematous patients in hot weather; appropriate therapy is water restriction, rather than administration of salt except in rare instances when the hyponatremia is life-threatening. In actual salt depletion, appropriate replacement is the therapy of choice.

Hyperuricemia may occur or frank gout may be precipitated in certain patients receiving thiazide therapy.

In diabetic patients dosage adjustments of insulin or oral hypoglycemic agents may be required. Hyperglycemia may occur with thiazide diuretics. Thus latent diabetes mellitus may become manifest during thiazide therapy.

The antihypertensive effects of the drug may be enhanced in the postsympathectomy patient.

If progressive renal impairment becomes evident consider withholding or discontinuing diuretic therapy.

Thiazides have been shown to increase the urinary excretion of magnesium; this may result in hypomagnesemia.

Thiazides may decrease urinary calcium excretion. Thiazides may cause intermittent and slight elevation of serum calcium in the absence of known disorders of calcium metabolism. Marked hypercalcemia may be evidence of hidden hyperparathyroidism. Thiazides should be discontinued before carrying out tests for parathyroid function.

Increases in cholesterol and triglyceride levels may be associated with thiazide diuretic therapy.

Information for Patients

Angioedema: Angioedema, including laryngeal edema may occur at any time during treatment with angiotensin-converting enzyme inhibitors, including ZESTORETIC. Patients should be so advised and told to report immediately any signs or symptoms suggesting angioedema (swelling of face, extremities, eyes, lips, tongue, difficulty in swallowing or breathing) and to take no more drug until they have consulted with the prescribing physician.

Symptomatic Hypotension: Patients should be cautioned to report lightheadedness especially during the first few days of therapy. If actual syncope occurs, the patients should be told to discontinue the drug until they have consulted with the prescribing physician.

All patients should be cautioned that excessive perspiration and dehydration may lead to an excessive fall in blood pressure because of reduction in fluid volume. Other causes of volume depletion such as vomiting or diarrhea may also lead to a fall in blood pressure; patients should be advised to consult with their physician.

Hyperkalemia: Patients should be told not to use salt substitutes containing potassium without consulting their physician.

Leukopenia/Neutropenia: Patients should be told to report promptly any indication of infection (e.g., sore throat, fever) which may be a sign of leukopenia/neutropenia.

Pregnancy: Female patients of childbearing age should be told about the consequences of exposure to ZESTORETIC during pregnancy. Discuss treatment options with women planning to become pregnant. Patients should be asked to report pregnancies to their physicians as soon as possible.

Non-melanoma Skin Cancer: Instruct patients taking hydrochlorothiazide to protect skin from the sun and undergo regular skin cancer screening.

NOTE: As with many other drugs, certain advice to patients being treated with ZESTORETIC is warranted. This information is intended to aid in the safe and effective use of this medication. It is not a disclosure of all possible adverse or intended effects.

Drug Interactions

Lisinopril

Hypotension - Patients on Diuretic Therapy: Patients on diuretics and especially those in whom diuretic therapy was recently instituted, may occasionally experience an excessive reduction of blood pressure after initiation of therapy with lisinopril. The possibility of hypotensive effects with lisinopril can be minimized by either discontinuing the diuretic or increasing the salt intake prior to initiation of treatment with lisinopril. If it is necessary to continue the diuretic, initiate therapy with lisinopril at a dose of 5 mg daily, and provide close medical supervision after the initial dose for at least two hours and until blood pressure has stabilized for at least an additional hour (see WARNINGS, and DOSAGE AND ADMINISTRATION). When a diuretic is added to the therapy of a patient receiving lisinopril, an additional antihypertensive effect is usually observed (see DOSAGE AND ADMINISTRATION).

Non-Steroidal Anti-Inflammatory Agents including Selective Cyclooxygenase-2 Inhibitors (COX-2 Inhibitors): In patients who are elderly, volume-depleted (including those on diuretic therapy), or with compromised renal function, co-administration of NSAIDs, including selective COX-2 inhibitors, with ACE inhibitors, including lisinopril, may result in deterioration of renal function, including possible acute renal failure. These effects are usually reversible. Monitor renal function periodically in patients receiving lisinopril and NSAID therapy.

The antihypertensive effect of ACE inhibitors, including lisinopril, may be attenuated by NSAIDs.

Dual Blockade of the Renin-Angiotensin System (RAS)
Dual blockade of the RAS with angiotensin receptor blockers, ACE inhibitors, or aliskiren is associated with increased risks of hypotension, hyperkalemia, and changes in renal function (including acute renal failure) compared to monotherapy.

The VA NEPHRON trial enrolled 1448 patients with type 2 diabetes, elevated urinary-albumin-to-creatinine ratio, and decreased estimated glomerular filtration rate (GFR 30 mL/min to 89.9 mL/min), randomized them to lisinopril or placebo on a background of losartan therapy and followed them for a median of 2.2 years. Patients receiving the combination of losartan and lisinopril did not obtain any additional benefit compared to monotherapy for the combined endpoint of decline in GFR, end state renal disease, or death, but experienced an increased incidence of hyperkalemia and acute kidney injury compared with the monotherapy group.

In general, avoid combined use of RAS inhibitors, closely monitor blood pressure, renal function and electrolytes in patients on ZESTORETIC and other agents that affect the RAS.

Do not co-administer aliskiren with ZESTORETIC in patients with diabetes. Avoid use of aliskiren with ZESTORETIC in patients with renal impairment (GFR < 60 mL/min).

Other Agents: Lisinopril has been used concomitantly with nitrates and/or digoxin without evidence of clinically significant adverse interactions. No meaningful clinically important pharmacokinetic interactions occurred when lisinopril was used concomitantly with propranolol, digoxin, or hydrochlorothiazide. The presence of food in the stomach does not alter the bioavailability of lisinopril.

Agents Increasing Serum Potassium: Lisinopril attenuates potassium loss caused by thiazide-type diuretics. Use of lisinopril with potassium-sparing diuretics (e.g., spironolactone, eplerenone, triamterene, or amiloride), potassium supplements, or potassium-containing salt substitutes may lead to significant increases in serum potassium. Therefore, if concomitant use of these agents is indicated, because of demonstrated hypokalemia, they should be used with caution and with frequent monitoring of serum potassium.

Lithium: Lithium toxicity has been reported in patients receiving lithium concomitantly with drugs which cause elimination of sodium, including ACE inhibitors. Lithium toxicity was usually reversible upon discontinuation of lithium and the ACE inhibitor. It is recommended that serum lithium levels be monitored frequently if lisinopril is administered concomitantly with lithium.

mTOR (mammalian target of rapamycin) inhibitors
Patients receiving coadministration of ACE inhibitor and mTOR inhibitor (e.g., temsirolimus, sirolimus, everolimus) therapy may be at increased risk for angioedema (see WARNINGS).

Neprilysin Inhibitors
Patients taking concomitant neprilysin inhibitors may be at increased risk for angioedema (see WARNINGS).

Hydrochlorothiazide

When administered concurrently the following drugs may interact with thiazide diuretics.

Alcohol, barbiturates, or narcotics - potentiation of orthostatic hypotension may occur.

Antidiabetic drugs (oral agents and insulin) - dosage adjustment of the antidiabetic drug may be required.

Other antihypertensive drugs - additive effect or potentiation.

Cholestyramine and colestipol resins - Absorption of hydrochlorothiazide is impaired in the presence of anionic exchange resins. Single doses of either cholestyramine or colestipol resins bind the hydrochlorothiazide and reduce its absorption from the gastrointestinal tract by up to 85% and 43%, respectively.

Corticosteroids, ACTH - intensified electrolyte depletion, particularly hypokalemia.

Pressor amines (e.g., norepinephrine) - possible decreased response to pressor amines but not sufficient to preclude their use.

Skeletal muscle relaxants, nondepolarizing (e.g., tubocurarine) - possible increased responsiveness to the muscle relaxant.

Lithium - should not generally be given with diuretics. Diuretic agents reduce the renal clearance of lithium and add a high risk of lithium toxicity. Refer to the package insert for lithium preparations before use of such preparations with ZESTORETIC.

Non-Steroidal Anti-inflammatory Drugs - In some patients, the administration of a non-steroidal anti-inflammatory agent can reduce the diuretic, natriuretic, and antihypertensive effects of loop, potassium-sparing and thiazide diuretics. Therefore, when ZESTORETIC and non-steroidal anti-inflammatory agents are used concomitantly, the patient should be observed closely to determine if the desired effect of ZESTORETIC is obtained.

Gold: Nitritoid reactions (symptoms include facial flushing, nausea, vomiting and hypotension) have been reported rarely in patients on therapy with injectable gold (sodium aurothiomalate) and concomitant ACE inhibitor therapy including ZESTORETIC.

Carcinogenesis, Mutagenesis, Impairment of Fertility

Lisinopril and Hydrochlorothiazide

Lisinopril in combination with hydrochlorothiazide was not mutagenic in a microbial mutagen test using Salmonella typhimurium (Ames test) or Escherichia coli with or without metabolic activation or in a forward mutation assay using Chinese hamster lung cells. Lisinopril and hydrochlorothiazide did not produce DNA single strand breaks in an in vitro alkaline elution rat hepatocyte assay. In addition, it did not produce increases in chromosomal aberrations in an in vitro test in Chinese hamster ovary cells or in an in vivo study in mouse bone marrow.

Lisinopril

There was no evidence of a tumorigenic effect when lisinopril was administered for 105 weeks to male and female rats at doses up to 90 mg/kg/day (about 56 or 9 times* the maximum daily human dose, based on body weight and body surface area, respectively). There was no evidence of carcinogenicity when lisinopril was administered for 92 weeks to (male and female) mice at doses up to 135 mg/kg/day (about 84 times* the maximum recommended daily human dose). This dose was 6.8 times the maximum human dose based on body surface area in mice.

*Calculations assume a human weight of 50 kg and human body surface area of 1.62m^2.

Lisinopril was not mutagenic in the Ames microbial mutagen test with or without metabolic activation. It was also negative in a forward mutation assay using Chinese hamster lung cells. Lisinopril did not produce single strand DNA breaks in an in vitro alkaline elution rat hepatocyte assay. In addition, lisinopril did not produce increases in chromosomal aberrations in an in vitro test in Chinese hamster ovary cells or in an in vivo study in mouse bone marrow.

There were no adverse effects on reproductive performance in male and female rats treated with up to 300 mg/kg/day of lisinopril. This dose is 188 times and 30 times the maximum daily human dose based on mg/kg and mg/m^2, respectively.

Hydrochlorothiazide

Two-year feeding studies in mice and rats conducted under the auspices of the National Toxicology Program (NTP) uncovered no evidence of a carcinogenic potential of hydrochlorothiazide in female mice (at doses of up to approximately 600 mg/kg/day) or in male and female rats (at doses of up to approximately 100 mg/kg/day). These doses are 150 times and 12 times for mice and 25 times and 4 times for rats the maximum human daily dose based on mg/kg and mg/m^2, respectively. The NTP, however, found equivocal evidence for hepatocarcinogenicity in male mice.

Hydrochlorothiazide was not genotoxic in vitro in the Ames mutagenicity assay of Salmonella typhimurium strains TA 98, TA 100, TA 1535, TA 1537, and TA 1538 and in the Chinese Hamster Ovary (CHO) test for chromosomal aberrations, or in vivo in assays using mouse germinal cell chromosomes, Chinese hamster bone marrow chromosomes, and the Drosophila sex-linked recessive lethal trait gene. Positive test results were obtained only in the in vitro CHO Sister Chromatid Exchange (clastogenicity) and in the Mouse Lymphoma Cell (mutagenicity) assays, using concentrations of hydrochlorothiazide from 43 mcg/mL to 1300 mcg/mL, and in the Aspergillus nidulans nondisjunction assay at an unspecified concentration.

Hydrochlorothiazide had no adverse effects on the fertility of mice and rats of either sex in studies wherein these species were exposed, via their diet, to doses of up to 100 mg/kg and 4 mg/kg, respectively, prior to conception and throughout gestation. In mice this dose is 25 times and 2 times the maximum daily human dose based on mg/kg and mg/m^2, respectively. In rats this dose is 1 times and 0.2 times the maximum daily human dose based on mg/kg and mg/m^2, respectively.

Nursing Mothers

It is not known whether lisinopril is excreted in human milk. However, milk of lactating rats contains radioactivity following administration of ^14C lisinopril. In another study, lisinopril was present in rat milk at levels similar to plasma levels in the dams. Thiazides do appear in human milk. Because of the potential for serious adverse reactions in nursing infants from ACE inhibitors and hydrochlorothiazide, a decision should be made whether to discontinue nursing and/or discontinue ZESTORETIC, taking into account the importance of the drug to the mother.

Pediatric Use

Neonates with a history of in utero exposure to ZESTORETIC:

If oliguria or hypotension occurs, direct attention toward support of blood pressure and renal perfusion. Exchange transfusions or dialysis may be required as a means of reversing hypotension and/or substituting for disordered renal function. Lisinopril, which crosses the placenta, has been removed from neonatal circulation by peritoneal dialysis with some clinical benefit, and theoretically may be removed by exchange transfusion, although there is no experience with the latter procedure.

Safety and effectiveness in pediatric patients have not been established.

Geriatric Use

Clinical studies of ZESTORETIC did not include sufficient numbers of subjects aged 65 and over to determine whether they respond differently from younger subjects. Other reported clinical experience has not identified differences in responses between the elderly and younger patients. In general, dose selection for an elderly patient should be cautious, usually starting at the low end of the dosing range, reflecting the greater frequency of decreased hepatic, renal, or cardiac function, and of concomitant disease or other drug therapy.

This drug is known to be substantially excreted by the kidney, and the risk of toxic reactions to this drug may be greater in patients with impaired renal function. Because elderly patients are more likely to have decreased renal function, care should be taken in dose selection. Evaluation of the hypertensive patient should always include assessment of renal function.

ADVERSE REACTIONS

ZESTORETIC has been evaluated for safety in 930 patients including 100 patients treated for 50 weeks or more.

In clinical trials with ZESTORETIC no adverse experiences peculiar to this combination drug have been observed. Adverse experiences that have occurred have been limited to those that have been previously reported with lisinopril or hydrochlorothiazide.

The most frequent clinical adverse experiences in controlled trials (including open label extensions) with any combination of lisinopril and hydrochlorothiazide were: dizziness (7.5%), headache (5.2%), cough (3.9%), fatigue (3.7%) and orthostatic effects (3.2%) all of which were more common than in placebo-treated patients. Generally, adverse experiences were mild and transient in nature, but see WARNINGS regarding angioedema and excessive hypotension or syncope. Discontinuation of therapy due to adverse effects was required in 4.4% of patients principally because of dizziness, cough, fatigue and muscle cramps.

Adverse experiences occurring in greater than one percent of patients treated with lisinopril plus hydrochlorothiazide in controlled clinical trials are shown below.

Percent of Patients in Controlled Studies

 | Lisinopril and Hydrochlorothiazide (n=930) Incidence (discontinuation) |  | Placebo (n=207) Incidence
Dizziness | 7.5 | (0.8) | 1.9
Headache | 5.2 | (0.3) | 1.9
Cough | 3.9 | (0.6) | 1.0
Fatigue | 3.7 | (0.4) | 1.0
Orthostatic Effects | 3.2 | (0.1) | 1.0
Diarrhea | 2.5 | (0.2) | 2.4
Nausea | 2.2 | (0.1) | 2.4
Upper Respiratory Infection | 2.2 | (0.0) | 0.0
Muscle Cramps | 2.0 | (0.4) | 0.5
Asthenia | 1.8 | (0.2) | 1.0
Paresthesia | 1.5 | (0.1) | 0.0
Hypotension | 1.4 | (0.3) | 0.5
Vomiting | 1.4 | (0.1) | 0.5
Dyspepsia | 1.3 | (0.0) | 0.0
Rash | 1.2 | (0.1) | 0.5
Impotence | 1.2 | (0.3) | 0.0

Clinical adverse experiences occurring in 0.3% to 1.0% of patients in controlled trials and rarer, serious, possibly drug-related events reported in marketing experience are listed below:

Body as a Whole: Chest pain, abdominal pain, syncope, chest discomfort, fever, trauma, virus infection. Cardiovascular: Palpitation, orthostatic hypotension. Digestive: Gastrointestinal cramps, dry mouth, constipation, heartburn. Musculoskeletal: Back pain, shoulder pain, knee pain, back strain, myalgia, foot pain. Nervous/Psychiatric: Decreased libido, vertigo, depression, somnolence. Respiratory: Common cold, nasal congestion, influenza, bronchitis, pharyngeal pain, dyspnea, pulmonary congestion, chronic sinusitis, allergic rhinitis, pharyngeal discomfort. Skin: Flushing, pruritus, skin inflammation, diaphoresis, cutaneous pseudolymphoma. Special Senses: Blurred vision, tinnitus, otalgia. Urogenital: Urinary tract infection.

Angioedema: Angioedema of the face, extremities, lips, tongue, glottis and/or larynx has been reported (see WARNINGS).

In rare cases, intestinal angioedema has been reported in post marketing experience.

Hypotension: In clinical trials, adverse effects relating to hypotension occurred as follows: hypotension (1.4%), orthostatic hypotension (0.5%), other orthostatic effects (3.2%). In addition syncope occurred in 0.8% of patients (see WARNINGS).

Cough: See PRECAUTIONS - Cough.

Clinical Laboratory Test Findings

Serum Electrolytes: (See PRECAUTIONS).

Creatinine, Blood Urea Nitrogen: Minor reversible increases in blood urea nitrogen and serum creatinine were observed in patients with essential hypertension treated with ZESTORETIC. More marked increases have also been reported and were more likely to occur in patients with renal artery stenosis (see PRECAUTIONS).

Serum Uric Acid, Glucose, Magnesium, Cholesterol, Triglycerides and Calcium: (See PRECAUTIONS).

Hemoglobin and Hematocrit: Small decreases in hemoglobin and hematocrit (mean decreases of approximately 0.5 g% and 1.5 vol%, respectively) occurred frequently in hypertensive patients treated with ZESTORETIC but were rarely of clinical importance unless another cause of anemia coexisted. In clinical trials, 0.4% of patients discontinued therapy due to anemia.

Liver Function Tests: Rarely, elevations of liver enzymes and/or serum bilirubin have occurred. (See WARNINGS, Hepatic Failure).

Other adverse reactions that have been reported with the individual components are listed below:

Lisinopril - In clinical trials adverse reactions which occurred with lisinopril were also seen with ZESTORETIC. In addition, and since lisinopril has been marketed, the following adverse reactions have been reported with lisinopril and should be considered potential adverse reactions for ZESTORETIC: Body as a Whole: Anaphylactoid reactions (see WARNINGS, Anaphylactoid Reactions During Membrane Exposure), malaise, edema, facial edema, pain, pelvic pain, flank pain, chills; Cardiovascular: Cardiac arrest, myocardial infarction or cerebrovascular accident, possibly secondary to excessive hypotension in high risk patients (see WARNINGS, Hypotension), pulmonary embolism and infarction, worsening of heart failure, arrhythmias (including tachycardia, ventricular tachycardia, atrial tachycardia, atrial fibrillation, bradycardia, and premature ventricular contractions), angina pectoris, transient ischemic attacks, paroxysmal nocturnal dyspnea, decreased blood pressure, peripheral edema, vasculitis; Digestive: Pancreatitis, hepatitis (hepatocellular or cholestatic jaundice) (see WARNINGS, Hepatic Failure), gastritis, anorexia, flatulence, increased salivation; Endocrine: Diabetes mellitus, inappropriate antidiuretic hormone secretion; Hematologic: Rare cases of bone marrow depression, hemolytic anemia, leukopenia/neutropenia, and thrombocytopenia have been reported in which a causal relationship to lisinopril can not be excluded; Metabolic: Gout, weight loss, dehydration, fluid overload, weight gain; Musculoskeletal: Arthritis, arthralgia, neck pain, hip pain, joint pain, leg pain, arm pain, lumbago; Nervous System/Psychiatric: Ataxia, memory impairment, tremor, insomnia, stroke, nervousness, confusion, peripheral neuropathy (e.g., paresthesia, dysesthesia), spasm, hypersomnia, irritability; mood alterations (including depressive symptoms); hallucinations; Respiratory: Malignant lung neoplasms, hemoptysis, pulmonary edema, pulmonary infiltrates, bronchospasm, asthma, pleural effusion, pneumonia, eosinophilic pneumonitis, wheezing, orthopnea, painful respiration, epistaxis, laryngitis, sinusitis, pharyngitis, rhinitis, rhinorrhea, chest sound abnormalities; Skin: Urticaria, alopecia, herpes zoster, photosensitivity, skin lesions, skin infections, pemphigus, erythema, psoriasis, rare cases of other severe skin reactions, including toxic epidermal necrolysis and Stevens-Johnson Syndrome (causal relationship has not been established); Special Senses: Visual loss, diplopia, photophobia, taste alteration, olfactory disturbance; Urogenital: Acute renal failure, oliguria, anuria, uremia, progressive azotemia, renal dysfunction (see PRECAUTIONS and DOSAGE AND ADMINISTRATION), pyelonephritis, dysuria, breast pain.

Miscellaneous: A symptom complex has been reported which may include a positive ANA, an elevated erythrocyte sedimentation rate, arthralgia/arthritis, myalgia, fever, vasculitis, eosinophilia and leukocytosis. Rash, photosensitivity or other dermatological manifestations may occur alone or in combination with these symptoms.

Hydrochlorothiazide - Body as a Whole: Weakness; Digestive: Anorexia, gastric irritation, cramping, jaundice (intrahepatic cholestatic jaundice) (see WARNINGS, Hepatic Failure), pancreatitis, sialoadenitis, constipation; Hematologic: Leukopenia, agranulocytosis, thrombocytopenia, aplastic anemia, hemolytic anemia; Musculoskeletal: Muscle spasm; Nervous System/Psychiatric: Restlessness; Renal: Renal failure, renal dysfunction, interstitial nephritis (see WARNINGS); Skin: Erythema multiforme including Stevens-Johnson Syndrome, exfoliative dermatitis including toxic epidermal necrolysis, alopecia; Special Senses: Xanthopsia; Hypersensitivity: Purpura, photosensitivity, urticaria, necrotizing angiitis (vasculitis and cutaneous vasculitis), respiratory distress including pneumonitis and pulmonary edema, anaphylactic reactions.

Postmarketing Experience

Non-melanoma Skin Cancer

Hydrochlorothiazide is associated with an increased risk of non-melanoma skin cancer. In a study conducted in the Sentinel System, increased risk was predominantly for squamous cell carcinoma (SCC) and in white patients taking large cumulative doses. The increased risk for SCC in the overall population was approximately 1 additional case per 16,000 patients per year, and for white patients taking a cumulative dose of ≥50,000mg the risk increase was approximately 1 additional SCC case for every 6,700 patients per year.

To report SUSPECTED ADVERSE REACTIONS, contact Almatica Pharma LLC at 1-877-447-7979 or FDA at 1-800-FDA-1088 or www.fda.gov/medwatch for voluntary reporting of adverse reactions.

OVERDOSAGE

No specific information is available on the treatment of overdosage with ZESTORETIC. Treatment is symptomatic and supportive. Therapy with ZESTORETIC should be discontinued and the patient observed closely. Suggested measures include induction of emesis and/or gastric lavage, and correction of dehydration, electrolyte imbalance and hypotension by established procedures.

Lisinopril

Following a single oral dose of 20 g/kg no lethality occurred in rats and death occurred in one of 20 mice receiving the same dose. The most likely manifestation of overdosage would be hypotension, for which the usual treatment would be intravenous infusion of normal saline solution.

Lisinopril can be removed by hemodialysis (see WARNINGS, Anaphylactoid Reaction During Membrane Exposure).

Hydrochlorothiazide

Oral administration of a single oral dose of 10 g/kg to mice and rats was not lethal. The most common signs and symptoms observed are those caused by electrolyte depletion (hypokalemia, hypochloremia, hyponatremia) and dehydration resulting from excessive diuresis. If digitalis has also been administered, hypokalemia may accentuate cardiac arrhythmias.

DOSAGE AND ADMINISTRATION

Lisinopril monotherapy is an effective treatment of hypertension in once-daily doses of 10 mg to 80 mg, while hydrochlorothiazide monotherapy is effective in doses of 12.5 mg per day to 50 mg per day. In clinical trials of lisinopril/hydrochlorothiazide combination therapy using lisinopril doses of 10 mg to 80 mg and hydrochlorothiazide doses of 6.25 mg to 50 mg, the antihypertensive response rates generally increased with increasing dose of either component.

The side effects (see WARNINGS) of lisinopril are generally rare and apparently independent of dose; those of hydrochlorothiazide are a mixture of dose-dependent phenomena (primarily hypokalemia) and dose-independent phenomena (e.g., pancreatitis), the former much more common than the latter. Therapy with any combination of lisinopril and hydrochlorothiazide may be associated with either or both dose-independent or dose-dependent side effects, but addition of lisinopril in clinical trials blunted the hypokalemia normally seen with diuretics.

To minimize dose-dependent side effects, it is usually appropriate to begin combination therapy only after a patient has failed to achieve the desired effect with monotherapy.

Dose Titration Guided by Clinical Effect: A patient whose blood pressure is not adequately controlled with either lisinopril or hydrochlorothiazide monotherapy may be switched to lisinopril/HCTZ 10/12.5 or lisinopril/HCTZ 20/12.5, depending on current monotherapy dose. Further increases of either or both components should depend on clinical response with blood pressure measured at the interdosing interval to ensure that there is an adequate antihypertensive effect at that time. The hydrochlorothiazide dose should generally not be increased until 2 to 3 weeks have elapsed. After addition of the diuretic it may be possible to reduce the dose of lisinopril. Patients whose blood pressures are adequately controlled with 25 mg of daily hydrochlorothiazide, but who experience significant potassium loss with this regimen may achieve similar or greater blood-pressure control without electrolyte disturbance if they are switched to lisinopril/HCTZ 10/12.5.

In patients who are currently being treated with a diuretic, symptomatic hypotension occasionally may occur following the initial dose of lisinopril. The diuretic should, if possible, be discontinued for two to three days before beginning therapy with lisinopril to reduce the likelihood of hypotension (see WARNINGS). If the patient's blood pressure is not controlled with lisinopril alone, diuretic therapy may be resumed.

If the diuretic cannot be discontinued, an initial dose of 5 mg of lisinopril should be used under medical supervision for at least two hours and until blood pressure has stabilized for at least an additional hour (see WARNINGS and PRECAUTIONS, Drug Interactions).

Concomitant administration of ZESTORETIC with potassium supplements, potassium salt substitutes or potassium-sparing diuretics may lead to increases of serum potassium (see PRECAUTIONS).

Replacement Therapy: The combination may be substituted for the titrated individual components.

Use in Renal Impairment: Regimens of therapy with lisinopril/HCTZ need not take account of renal function as long as the patient's creatinine clearance is >30 mL/min/1.7m^2 (serum creatinine roughly ≤3 mg/dL or 265 μmol/L). In patients with more severe renal impairment, loop diuretics are preferred to thiazides, so lisinopril/HCTZ is not recommended (see WARNINGS, Anaphylactoid Reactions During Membrane Exposure).

HOW SUPPLIED

ZESTORETIC 10-12.5 Tablets: Peach, round, biconvex, uncoated tablets identified with "141" debossed on one side and "ZESTORETIC" on the other side are supplied in bottles of 90 tablets (NDC 52427-435-90).

ZESTORETIC 20-12.5 Tablets: White, round, biconvex, uncoated tablets identified with "142" debossed on one side and "ZESTORETIC" on the other side are supplied in bottles of 90 tablets (NDC 52427-436-90).

ZESTORETIC 20-25 Tablets: Peach, round, biconvex, uncoated tablets identified with “145” debossed on one side and "ZESTORETIC" on the other side are supplied in bottles of 90 tablets (NDC 52427-437-90).

Storage

Store at controlled room temperature, 20°C to 25°C (68°F to 77°F) [see USP]. Protect from excessive light and humidity.

*AN69 is a registered trademark of Hospal Ltd.

ZESTORETIC is a trademark of Alvogen AZ IP Holdings LLC.

Product of USA

Distributed by:
Almatica Pharma LLC
Morristown, NJ 07960 USA

PI435-10
Rev. 03/2025

PACKAGE LABEL

NDC 52427-435-90

Rx only

ZESTORETIC® 10/12.5
(lisinopril/hydrochlorothiazide)

Each tablet contains:
10 mg lisinopril, USP and
12.5 mg hydrochlorothiazide, USP

90 tablets

PACKAGE LABEL

NDC 52427-436-90

Rx only

ZESTORETIC® 20/12.5
(lisinopril/hydrochlorothiazide)

Each tablet contains:
20 mg lisinopril, USP and
12.5 mg hydrochlorothiazide, USP

90 tablets

PACKAGE LABEL

NDC 52427-437-90

Rx only

ZESTORETIC® 20/25
(lisinopril/hydrochlorothiazide)

Each tablet contains:
20 mg lisinopril, USP and
25 mg hydrochlorothiazide, USP

90 tablets